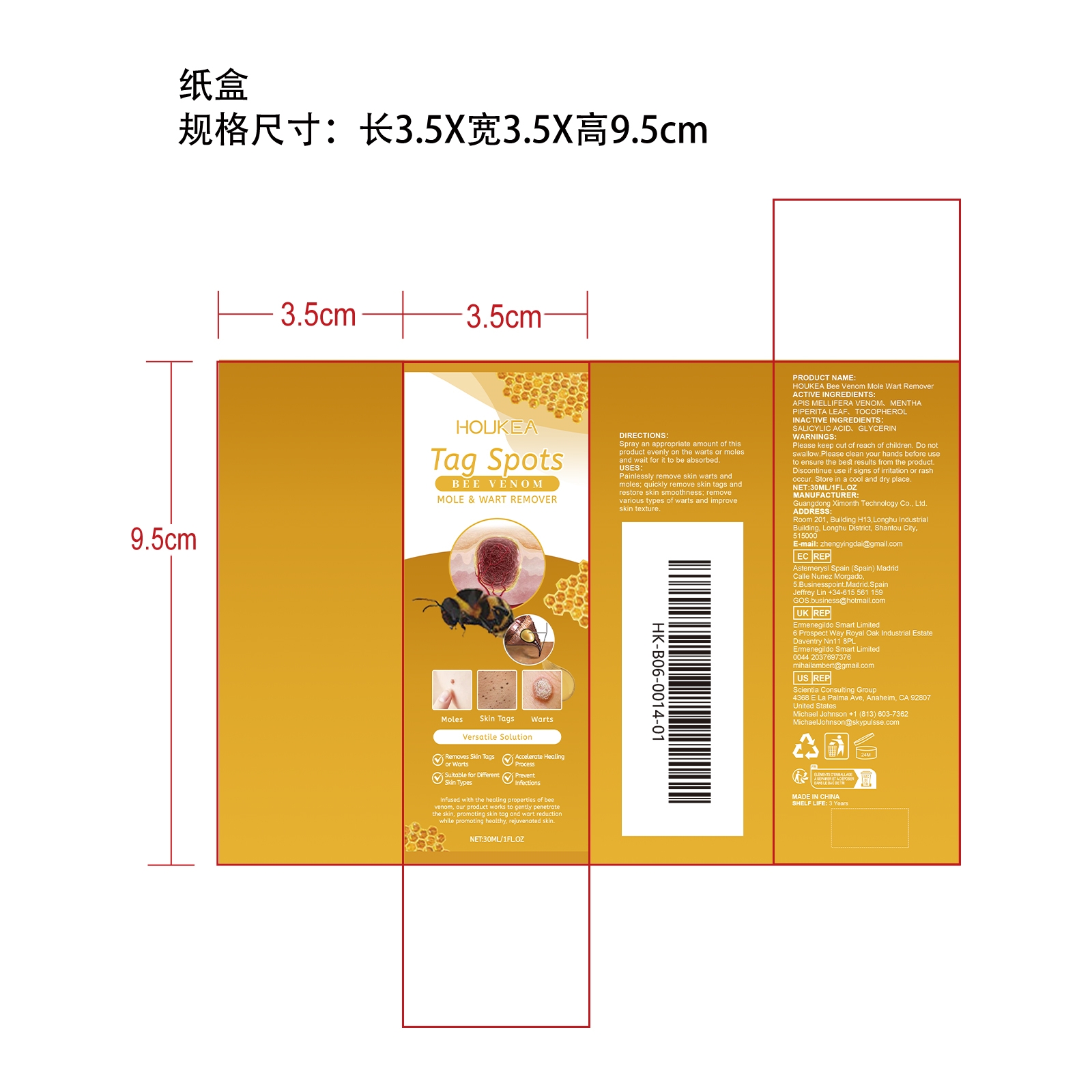 DRUG LABEL: HOUKEA Bee Venom Mole Wart Remover
NDC: 84660-104 | Form: SPRAY
Manufacturer: Guangdong Ximonth Technology Co., Ltd.
Category: otc | Type: HUMAN OTC DRUG LABEL
Date: 20241102

ACTIVE INGREDIENTS: MENTHA PIPERITA LEAF 3 mg/30 mg; APIS MELLIFERA VENOM 9 mg/30 mg; TOCOPHEROL 4.5 mg/30 mg
INACTIVE INGREDIENTS: GLYCERIN 9 mg/30 mg; SALICYLIC ACID 4.5 mg/30 mg

ACTIVE INGREDIENTS

APIS MELLIFERA VENOM,MENTHA PIPERITA LEAF,TOCOPHEROL

PURPOSE

Painlessly remove skin warts and moles; quickly remove skin tags and restore skin smoothness; remove various types of warts and improve skin texture.

USES

Spray an appropriate amount of this product evenly on the warts or moles and wait for it to be absorbed.

WARNINGS

Please keep out of reach of children.Do not swallow.Please clean your hands before use to ensure the best results from the product.Discontinue use if signs of irritation or rash occur.Store in a cool and dry place.

STOP USE

Discontinue use if signs of irritation or rash occur.

Do not use

Discontinue use if signs of irritation or rash occur.

KEEP OUT OF REACH OF CHILDREN

Please keep out of reach of children.Do not swallow.

STORAGE AND HANDLING

Store in a cool and dry place.

INACTIVE INGREDIENT

GLYCERIN、SALICYLIC ACID